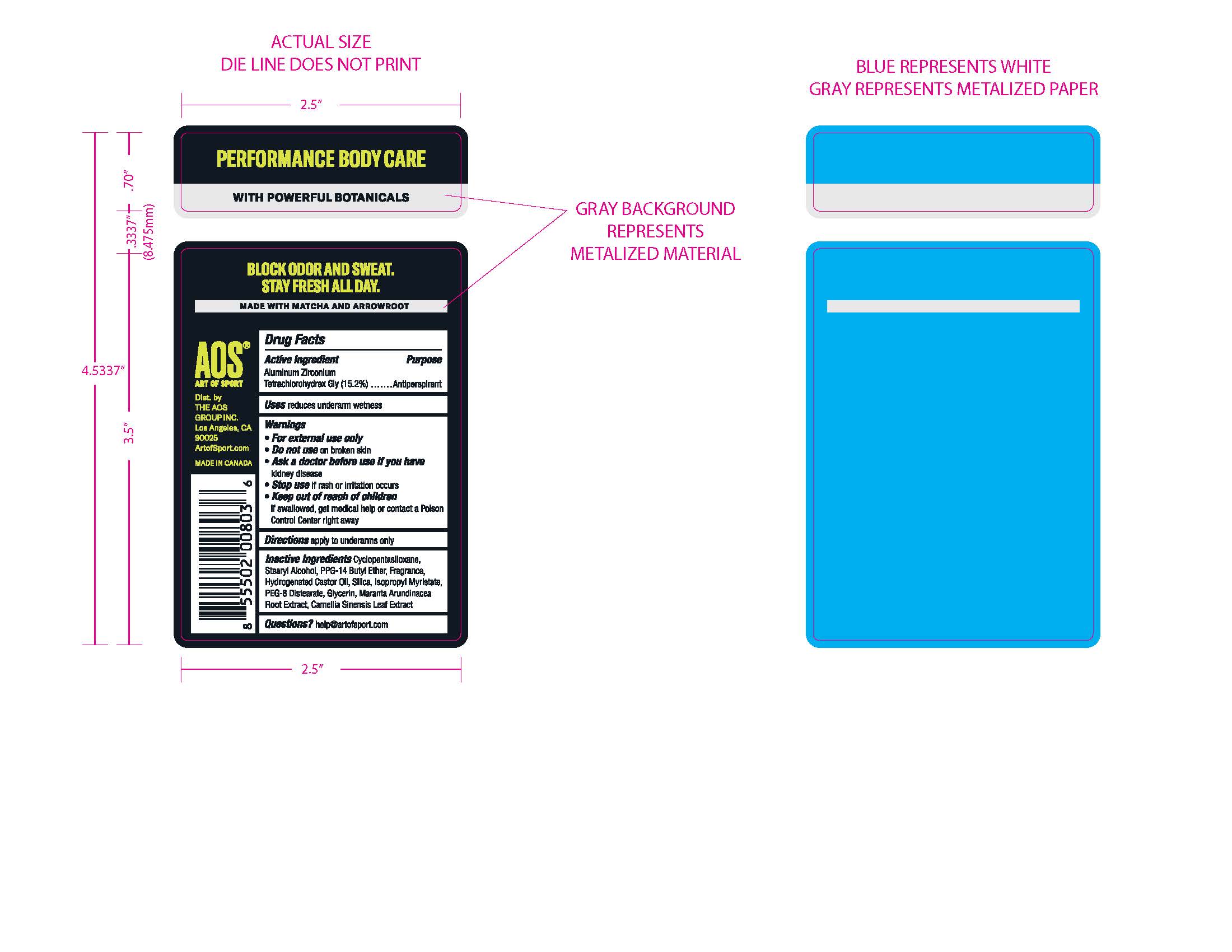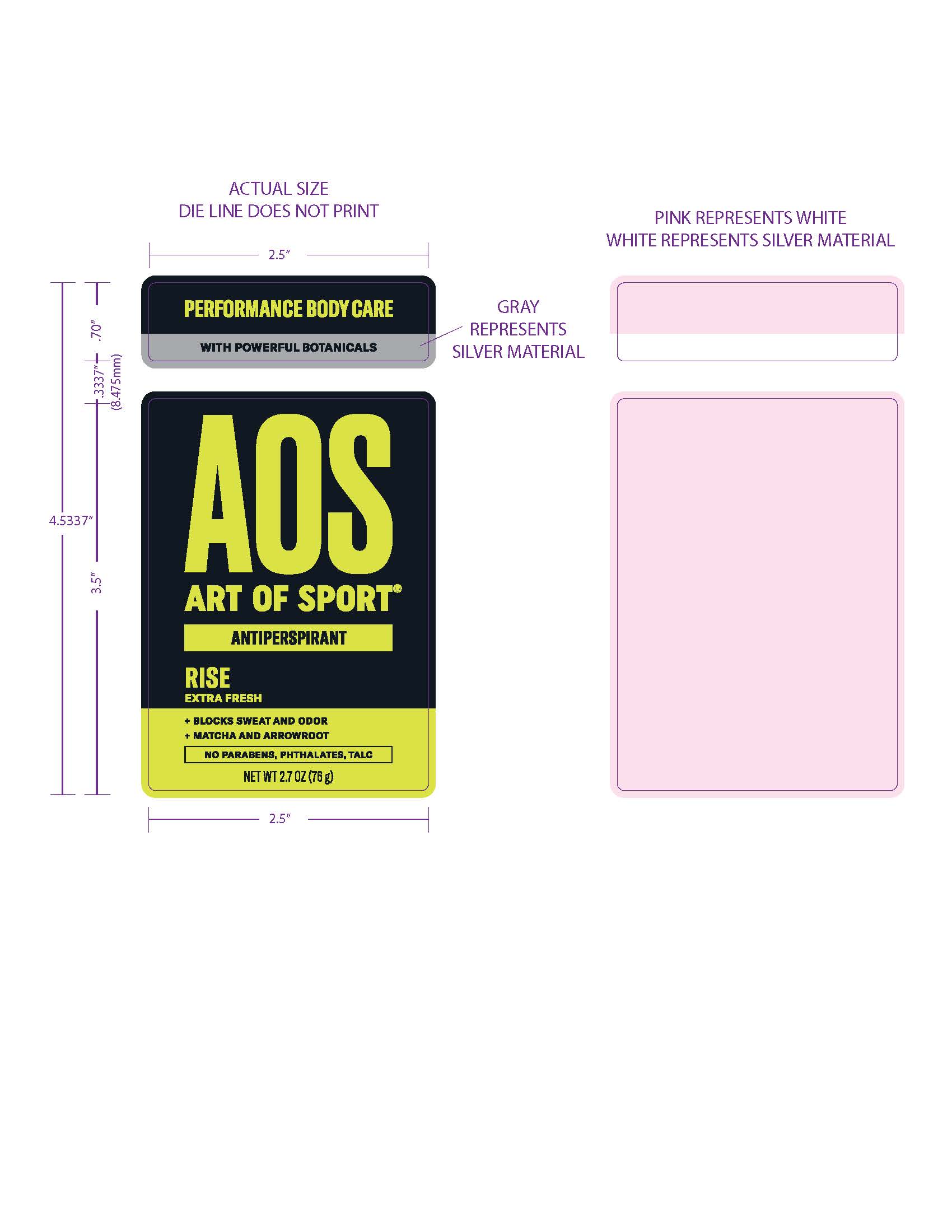 DRUG LABEL: ART OF SPORT ANTIPERSPIRANT RISE
NDC: 72698-505 | Form: STICK
Manufacturer: AOS GROUP INC, THE
Category: otc | Type: HUMAN OTC DRUG LABEL
Date: 20230130

ACTIVE INGREDIENTS: ALUMINUM ZIRCONIUM TETRACHLOROHYDREX GLY 15.2 g/100 g
INACTIVE INGREDIENTS: CYCLOMETHICONE 5; HYDROGENATED CASTOR OIL; SILICON DIOXIDE; GLYCERIN; MARANTA ARUNDINACEA ROOT; STEARYL ALCOHOL; ISOPROPYL MYRISTATE; GREEN TEA LEAF; PPG-14 BUTYL ETHER; PEG-8 DISTEARATE

Antiperspirant. Rise flavor.

Active Ingredient

Aluminum Zirconium Tetrachlorohydrex Gly (15.2%)

Purpose
Antiperspirant

Uses
reduces underarm wetness

Warnings
* For external use only
* Do not use on broken skin
* Ask a doctor before use if you have
kidney disease
* Stop use if rash or irritation occurs

* Keep out of reach of children
If swallowed, get medical help or contact a Poison Control Center right away

Directions
apply to underarms only

Inactive Ingredients
Cyclopentasiloxane, Stearyl Alcohol, PPG-14 Butyl Ether, Fragrance, Hydrogenated Castor Oil, Silica, Isorpropyl Myristate, PEG-8 Distearate, Glycerin, Maranta Arundinacea Root Extract, Camellia Sinensis Leaf Extract

Questions?
help@artofsport.com